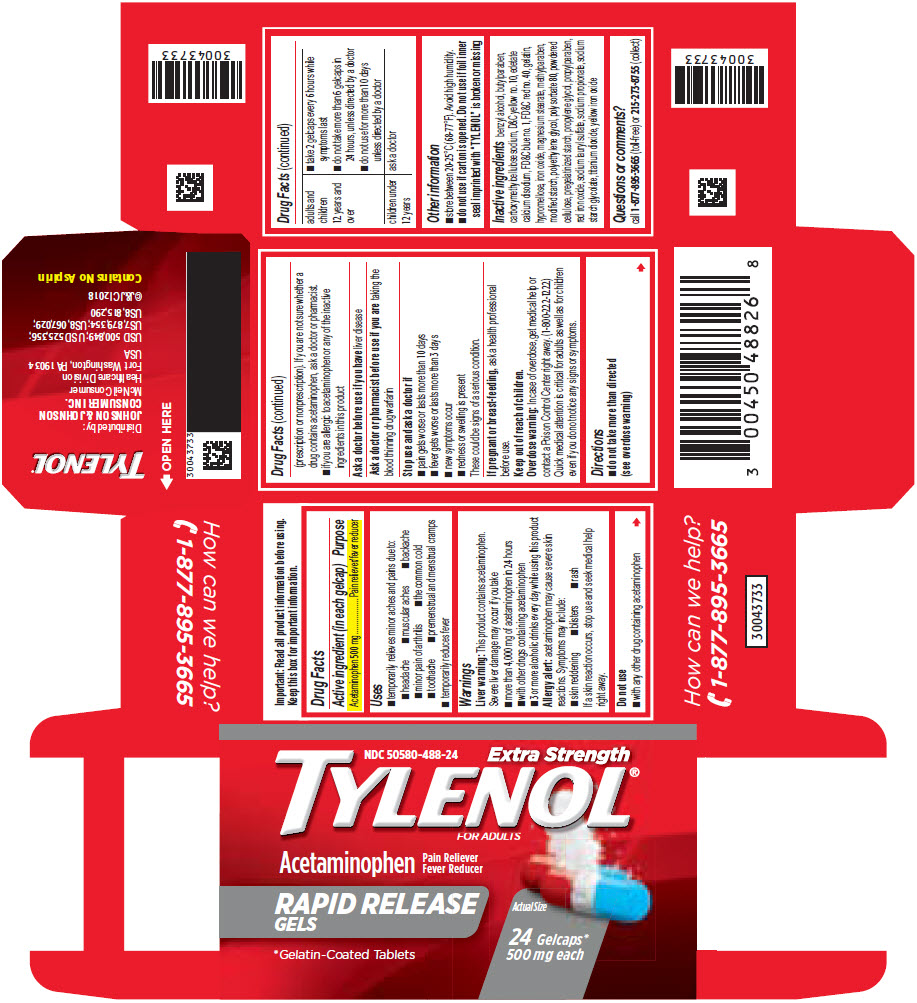 DRUG LABEL: TYLENOL
NDC: 50580-488 | Form: TABLET, COATED
Manufacturer: Kenvue Brands LLC
Category: otc | Type: HUMAN OTC DRUG LABEL
Date: 20250821

ACTIVE INGREDIENTS: ACETAMINOPHEN 500 mg/1 1
INACTIVE INGREDIENTS: BENZYL ALCOHOL; BUTYLPARABEN; CARBOXYMETHYLCELLULOSE SODIUM, UNSPECIFIED FORM; D&C YELLOW NO. 10; EDETATE CALCIUM DISODIUM; FD&C BLUE NO. 1; FD&C RED NO. 40; GELATIN, UNSPECIFIED; HYPROMELLOSE, UNSPECIFIED; FERROSOFERRIC OXIDE; MAGNESIUM STEARATE; METHYLPARABEN; POLYETHYLENE GLYCOL, UNSPECIFIED; POLYSORBATE 80; POWDERED CELLULOSE; PROPYLENE GLYCOL; PROPYLPARABEN; FERRIC OXIDE RED; SODIUM LAURYL SULFATE; SODIUM PROPIONATE; SODIUM STARCH GLYCOLATE TYPE A; TITANIUM DIOXIDE; FERRIC OXIDE YELLOW

TYLENOL
Extra strength

Drug Facts

Active ingredient (in each gelcap)

Acetaminophen 500 mg

Purpose

Pain reliever/fever reducer

Uses

- temporarily relieves minor aches and pains due to:
  - headache
  - muscular aches
  - backache
  - minor pain of arthritis
  - the common cold
  - toothache
  - premenstrual and menstrual cramps
- temporarily reduces fever

Warnings

Liver warning

This product contains acetaminophen. Severe liver damage may occur if you take

- more than 4,000 mg of acetaminophen in 24 hours
- with other drugs containing acetaminophen
- 3 or more alcoholic drinks every day while using this product

Allergy alert: acetaminophen may cause severe skin reactions. Symptoms may include:

- skin reddening
- blisters
- rash

If a skin reaction occurs, stop use and seek medical help right away.

Do not use

- with any other drug containing acetaminophen (prescription or nonprescription). If you are not sure whether a drug contains acetaminophen, ask a doctor or pharmacist.
- if you are allergic to acetaminophen or any of the inactive ingredients in this product

Ask a doctor before use if you have liver disease

Ask a doctor or pharmacist before use if you are taking the blood thinning drug warfarin

Stop use and ask a doctor if

- pain gets worse or lasts more than 10 days
- fever gets worse or lasts more than 3 days
- new symptoms occur
- redness or swelling is present

These could be signs of a serious condition.

PREGNANCY OR BREAST FEEDING

If pregnant or breast-feeding, ask a health professional before use.

Keep out of reach of children.

Overdose warning

In case of overdose, get medical help or contact a Poison Control Center right away. (1-800-222-1222) Quick medical attention is critical for adults as well as for children even if you do not notice any signs or symptoms.

Directions

- do not take more than directed
  (see overdose warning)

adults and children 12 years and over | - take 2 gelcaps every 6 hours while symptoms last - do not take more than 6 gelcaps in 24 hours, unless directed by a doctor - do not use for more than 10 days unless directed by a doctor
children under 12 years | ask a doctor

Other information

- store between 20-25°C (68-77°F). Avoid high humidity.
- do not use if carton is opened. Do not use if foil inner seal imprinted with "TYLENOL" is broken or missing

Inactive ingredients

benzyl alcohol, butylparaben, carboxymethylcellulose sodium, D&C yellow no. 10, edetate calcium disodium, FD&C blue no. 1, FD&C red no. 40, gelatin, hypromellose, iron oxide, magnesium stearate, methylparaben, modified starch, polyethylene glycol, polysorbate 80, powdered cellulose, pregelatinized starch, propylene glycol, propylparaben, red iron oxide, sodium lauryl sulfate, sodium propionate, sodium starch glycolate, titanium dioxide, yellow iron oxide

Questions or comments?

call 1-877-895-3665 (toll-free) or 215-273-8755 (collect)

PRINCIPAL DISPLAY PANEL

NDC 50580-488-24

Extra Strength
TYLENOL®
FOR ADULTS

Acetaminophen
Pain Reliever
Fever Reducer

RAPID RELEASE
GELS

Actual Size

24 Gelcaps*
500 mg each

*Gelatin-Coated Tablets